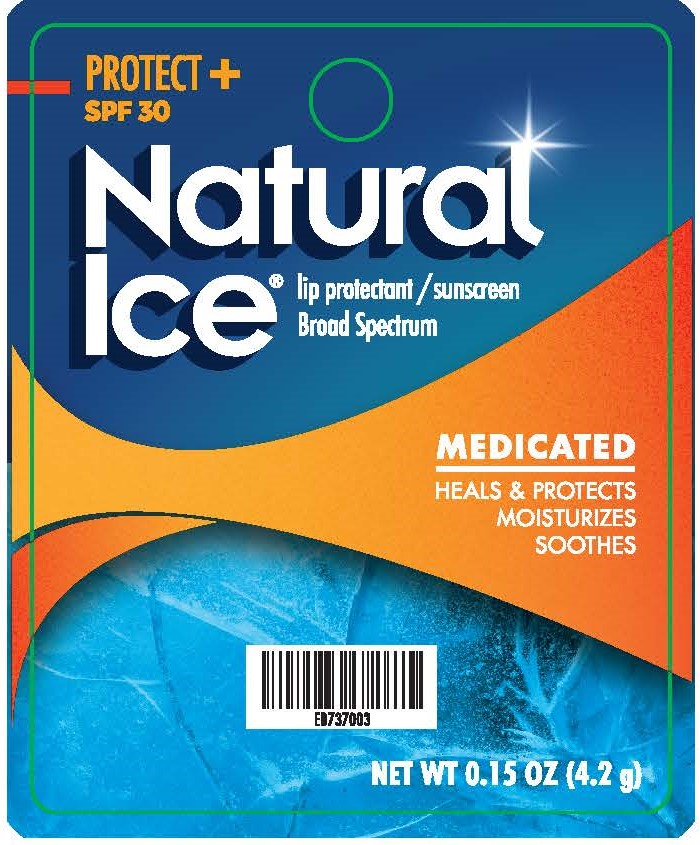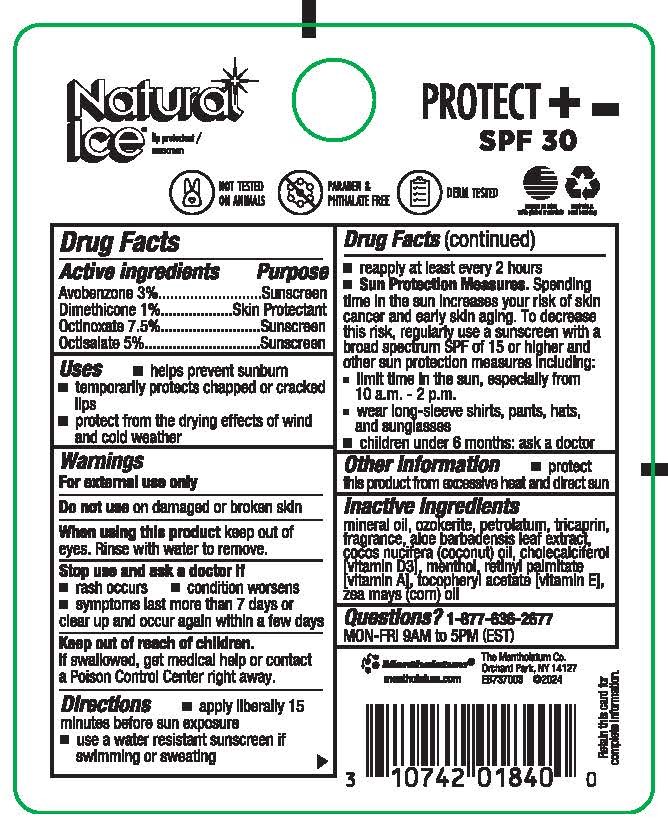 DRUG LABEL: Mentholatum Natural Ice Protect Plus SPF 30
NDC: 10742-3080 | Form: STICK
Manufacturer: The Mentholatum Company
Category: otc | Type: HUMAN OTC DRUG LABEL
Date: 20250620

ACTIVE INGREDIENTS: OCTINOXATE 75 mg/1 g; OCTISALATE 50 mg/1 g; AVOBENZONE 30 mg/1 g; DIMETHICONE 10 mg/1 g
INACTIVE INGREDIENTS: PETROLATUM; MENTHOL, (+)-; RETINYL PALMITATE; ALOE BARBADENSIS LEAF; ZEA MAYS (CORN) OIL; MINERAL OIL; CERESIN; TRICAPRIN; .ALPHA.-TOCOPHEROL ACETATE; CHOLECALCIFEROL; COCOS NUCIFERA (COCONUT) OIL; FRAGRANCE 13576

Drug Facts - Mentholatum Natural Ice Protect + SPF 30

Active ingredients

Avobenzone 3%
Dimethicone 1%
Octinoxate 7.5%
Octisalate 5%

Purpose

Avobenzone - Sunscreen
Dimethicone - Skin protectant
Octinoxate - Sunscreen
Octisalate - Sunscreen

Uses

- helps prevent sunburn
- temporarily protects chapped or cracked lips
- protect from the drying effects of wind and cold weather

Warnings

For external use only

Do not use

on damaged or broken skin

When using this product

keep out of eyes. Rinse with water to remove.

Stop use and ask a doctor if

- rash occurs
- condition worsens
- symptoms last more than 7 days or clear up and occur again within a few days

Keep out of reach of children

If swallowed, get medical help or contact a Poison Control Center right away.

Directions

- apply liberally 15 minutes before sun exposure
- use a water resistant sunscreen if swimming or sweating
- reapply at least every 2 hours

Sun Protection Measures. Spending time in the sun increases your risk of skin cancer and early skin aging. To decrease this risk, regularly use a sunscreen with a broad spectrum SPF of 15 or higher and other sun protection measures including:
limit time in the sun, especially from 10 a.m. – 2 p.m.
wear long-sleeve shirts, pants, hats, and sunglasses
children under 6 months: ask a doctor

Other Information

- protect this product from excessive heat and direct sun

Inactive ingredients

mineral oil, ozokerite, petrolatum, tricaprin, fragrance, aloe barbadensis leaf extract, cocos nucifera (coconut) oil, cholecalciferol [vitamin D3], menthol, retinyl palmitate [vitamin A], tocopheryl acetate [vitamin E], zea mays (corn) oil

Questions?

1-877-636-2677

MON-FRI 9AM to 5PM (EST)

mentholatum.com